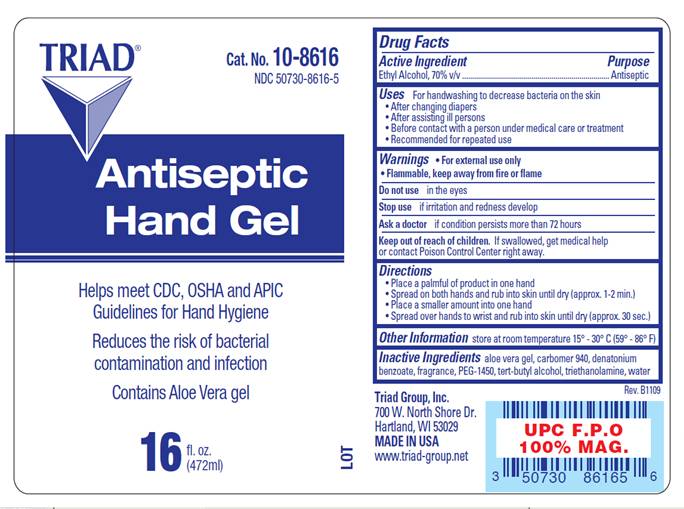 DRUG LABEL: Antiseptic Hand Gel
NDC: 50730-8616 | Form: GEL
Manufacturer: H and P Industries, Inc. dba Triad Group
Category: otc | Type: HUMAN OTC DRUG LABEL
Date: 20091123

ACTIVE INGREDIENTS: alcohol .70 mL/1 mL
INACTIVE INGREDIENTS: aloe vera leaf; carbomer homopolymer type c; denatonium benzoate; polyethylene glycol 1450; tert-butyl alcohol; trolamine; water

DRUG FACTS

ACTIVE INGREDIENT

Ethyl Alcohol, 70% v/v

PURPOSE

Antiseptic

USES

For handwashing when water is not available to decrease bacteria on the skin

- after changing diapers
- after assisting ill persons
- before contact with a person under medical care or treatment
- recommended for repeated use

WARNINGS

For external use only.
Flammable, keep away from fire or flame.

Do not use

in the eyes.

Stop use and ask a doctor

- if irritation and redness develop.
- if condition persists for more than 72 hours

Keep out of reach of children

If swallowed, get medical help or contact a Poison Control Center right away.

DIRECTIONS

- Place a palmful of product in one hand
- Spread on both hands and rub into skin until dry (approx. 1-2 min.)
- Place a smaller amount into one hand
- Spread over hands to wrist and rub into skin until dry (approx. 30 sec.)

OTHER INFORMATION

Store at room temperature: 15°- 30° C (59° - 86° F)

INACTIVE INGREDIENTS

aloe vera gel, carbomer 940, denatonium benzoate, fragrance, PEG-1450, tert-butyl alcohol, triethanolamine, water

LABEL INFORMATION

Triad®
Cat. No. 10-8616
NDC 50730-8616-5
Antiseptic
Hand Gel
Reduces the risk of bacterial contamination and infection
Helps meet CDC, OSHA and APIC Guidelines for Hand Hygiene
Contains Aloe Vera Gel
Triad Group, Inc.
700 West North Shore Drive
Hartland, WI 53029
MADE IN USA
www.triad-group.net
16 fl. oz. (472 ml)